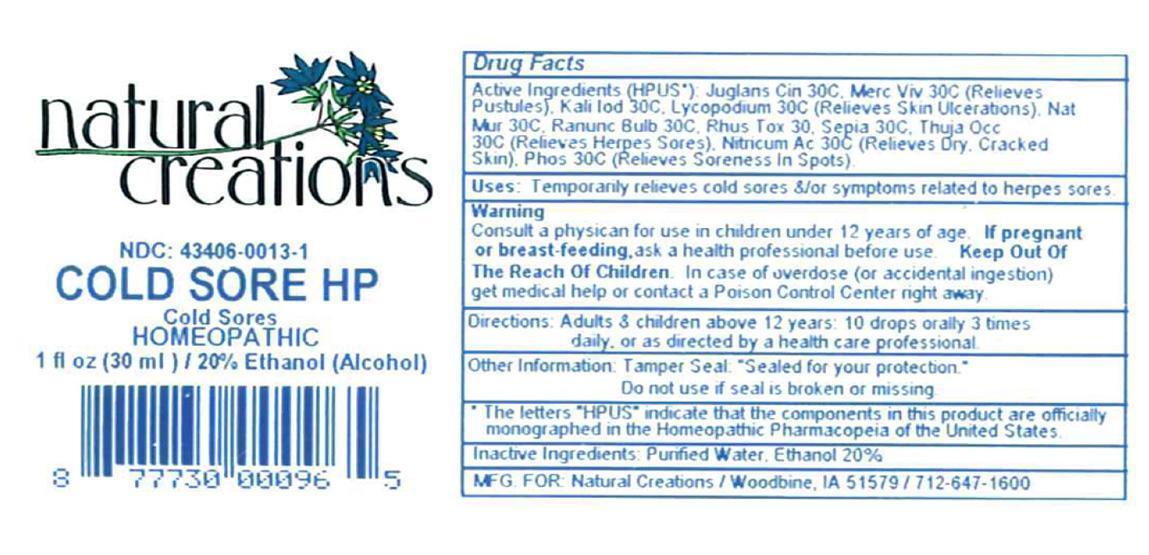 DRUG LABEL: Cold Sore HP
NDC: 43406-0013 | Form: LIQUID
Manufacturer: Natural Creations, Inc.
Category: homeopathic | Type: HUMAN OTC DRUG LABEL
Date: 20121018

ACTIVE INGREDIENTS: JUGLANS CINEREA BRANCH BARK/ROOT BARK 30 [hp_C]/1 mL; POTASSIUM IODIDE 30 [hp_C]/1 mL; LYCOPODIUM CLAVATUM SPORE 30 [hp_C]/1 mL; MERCURY 30 [hp_C]/1 mL; SODIUM CHLORIDE 30 [hp_C]/1 mL; NITRIC ACID 30 [hp_C]/1 mL; PHOSPHORUS 30 [hp_C]/1 mL; RANUNCULUS BULBOSUS 30 [hp_C]/1 mL; TOXICODENDRON PUBESCENS LEAF 30 [hp_C]/1 mL; SEPIA OFFICINALIS JUICE 30 [hp_C]/1 mL; THUJA OCCIDENTALIS LEAFY TWIG 30 [hp_C]/1 mL
INACTIVE INGREDIENTS: WATER; ALCOHOL

COLD SORE HP

ACTIVE INGREDIENT

ACTIVE INGREDIENTS (HPUS*): Juglans Cinerea 30C, Kali Iodatum 30C, Lycopodium Clavatum 30C, Mercurius Vivus 30C, Natrum Muriaticum 30C, Nitricum Acidum 30C, Phosphorus 30C, Ranunculus Bulbosus 30C, Rhus Toxicodendron 30C, Sepia 30C, Thuja Occidentalis 30C

INDICATIONS AND USAGE

USES: Temporarily relieves pustules, skin ulcerations, dry cracked skin with soreness, &/or symptoms related to herpes sores.

WARNING:

Consult a physician for use in children under 12 years of age. IF PREGNANT OR BREAST-FEEDING, ask a health care professional before use. KEEP OUT OF THE REACH OF CHILDREN. In case of overdose (or accidental ingestion) get medical help or contact a Poison Control Center right away.

DOSAGE AND ADMINISTRATION

DIRECTIONS: Adults and children above 12 years: 10 drops orally 3 times daily, or as directed by a health care professional.

OTHER INFORMATION: Tamper Seal: "Sealed for your protection."

Do not use if seal is broken or missing.

REFERENCES

*The letters "HPUS" indicate the components in the product are officially monographed in the Homeopathic Pharmacopeia of the United States.

INACTIVE INGREDIENTS: Purified Water, USP Ethanol Alcohol 20%

QUESTIONS AND COMMENTS?

MFG FOR: Natural Creations / Woodbine, IA / 51579 712.647.1600

LOT:

PURPOSE

USES: Temporarily relieves pustules, skin ulcerations, dry cracked skin with soreness, &/or symptoms related to herpes sores.

KEEP OUT OF REACH OF CHILDREN

KEEP OUT OF THE REACH OF CHILDREN. In case of overdose (or accidental ingestion (get medical help or contact a Poison Control Center.

PACKAGE LABEL

NDC: 43406-0013-1

COLD SORE HP

Cold Sores

1 fl oz (30 mL) / 20% Ethanol

UPC: 877730000965